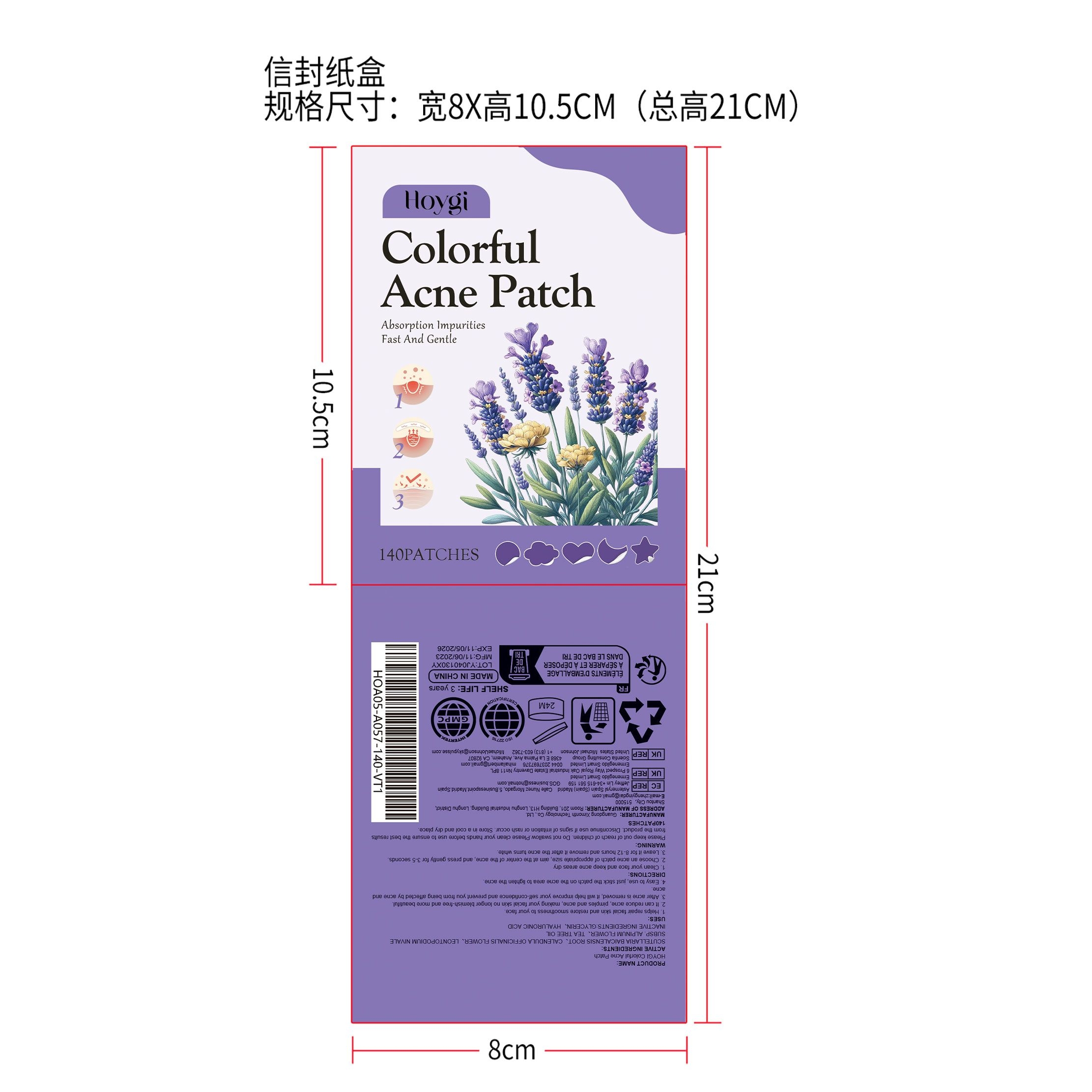 DRUG LABEL: HOYGI Colorful Acne Patch
NDC: 84660-061 | Form: PATCH
Manufacturer: Guangdong Ximonth Technology Co., Ltd.
Category: otc | Type: HUMAN OTC DRUG LABEL
Date: 20241101

ACTIVE INGREDIENTS: SCUTELLARIA BAICALENSIS ROOT 1 g/11 g; TEA TREE OIL 2 g/11 g; LEONTOPODIUM NIVALE SUBSP. ALPINUM FLOWER 2 g/11 g; CALENDULA OFFICINALIS FLOWER 2 g/11 g
INACTIVE INGREDIENTS: GLYCERIN 3 g/11 g; HYALURONIC ACID 1 g/11 g

Active Ingredient(s)

TEA TREE OIL、CALENDULA OFFICINALIS FLOWER、SCUTELLARIA BAICALENSIS ROOT、LEONTOPODIUM NIVALE SUBSP. ALPINUM FLOWER

Purpose

1. Helps repair facial skin and restore smoothness to your face.
2. It can reduce acne, pimples and acne, making your facial skin no longer blemish-free and more beautiful.
3. After acne is removed, it will help improve your self-confidence and prevent you from being affected by acne and acne.
4. Easy to use, just stick the patch on the acne area to lighten the acne.

Use

1. Clean your face and keep acne areas dry.
2. Choose an acne patch of appropriate size, aim at the center of the acne, and press gently for 3-5 secands.
3. Leave it for 8-12 hours and remove it after the acne turns white.

WARNINGS

Please keep out of reach of children.Do not swallow.Please clean your hands before use to ensure the best results from the product.Discontinue use if signs of irritation or rash occur.Store in a cool and dry place.

Do not use

Discontinue use if signs of irritation or rash occur.

Stop Use

Discontinue use if signs of irritation or rash occur.

KEEP OUT OF REACH OF CHILDREN

Please keep out of reach of children. Do not swallow.

STORAGE AND HANDLING

Store in a cool and dry place.

INACTIVE INGREDIENT

GLYCERIN、HYALURONIC ACID